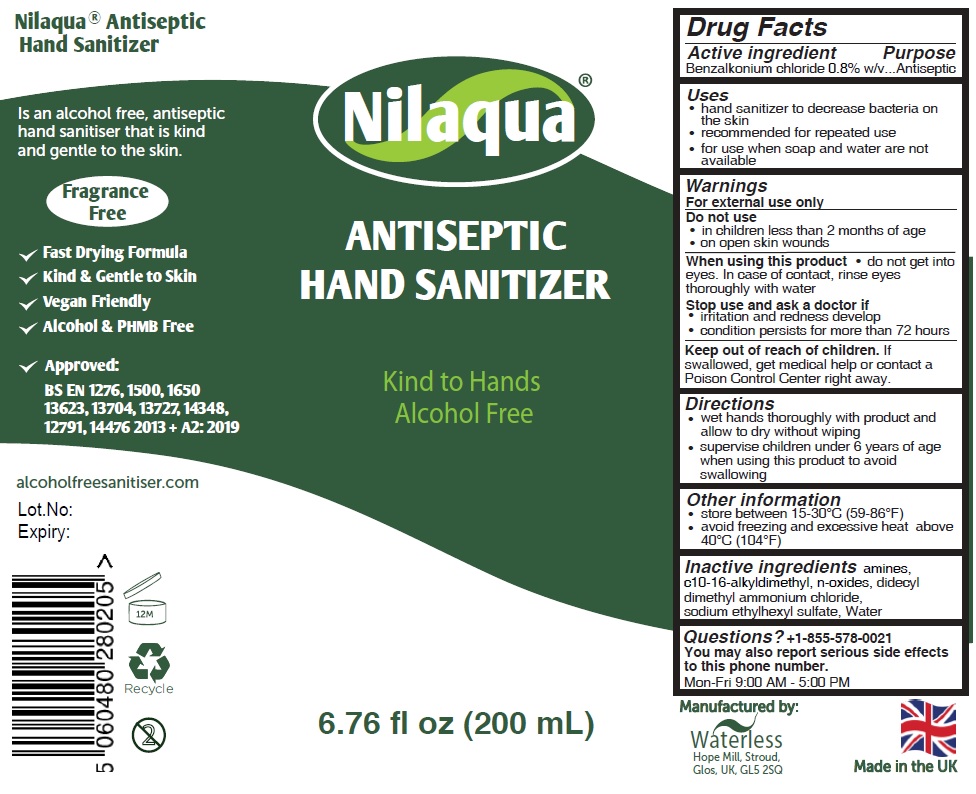 DRUG LABEL: Nilaqua ANTISEPTIC HAND SANITIZER FOAM
NDC: 80349-102 | Form: LIQUID
Manufacturer: WATERLESS LIMITED
Category: otc | Type: HUMAN OTC DRUG LABEL
Date: 20201107

ACTIVE INGREDIENTS: BENZALKONIUM CHLORIDE 0.8 g/100 mL
INACTIVE INGREDIENTS: (C10-C16)ALKYLDIMETHYLAMINE OXIDE; DIDECYLDIMONIUM CHLORIDE; SODIUM ETHASULFATE; WATER

Nilaqua® ANTISEPTIC HAND SANITIZER

Active ingredient

Benzalkonium chloride 0.8% w/v

Purpose

Antiseptic

Uses

- hand sanitizer to decrease bacteria on the skin
- recommended for repeated use
- for use when soap and water are not available

Warnings

For external use only

Do not use

- in children less than 2 months of age
- on open skin wounds

When using this product • do not get into eyes. In case of contact, rinse eyes thoroughly with water

Stop use and ask a doctor if

- irritation and redness develop
- condition persists for more than 72 hours

Keep out of reach of children. If swallowed, get medical help or contact a Poison Control Center right away.

Directions

- wet hands thoroughly with product and allow to dry without wiping
- supervise children under 6 years of age when using this product to avoid swallowing

Other information

- store between 15-30°C (59-86°F)
- avoid freezing and excessive heat above 40°C (104°F)

Inactive ingredients

amines, c10-16-alkyldimethyl, n-oxides, didecyl dimethyl ammonium chloride, sodium ethylhexyl sulfate, water

Questions? +1-855-578-0021

You may also report serious side effects to this phone number. Mon-Fri 9:00 AM - 5:00 PM

Kind to Hands

Nilaqua®Antiseptic Hand Sanitizer

Is an alcohol free, antiseptic hand sanitiser that is kind and gentle to the skin.

- Fragrance Free
- Fast Drying Formula
- Kind & Gentle to Skin
- Vegan Friendly
- Alcohol & PHMB Free

Approved:
BS EN 1276, 1500, 1650
13623, 13704, 13727, 14348,
12791, 14476 2013 +A2:2019

alcoholfreesanitiser.com.√

Recycle

Manufactured by: Waterless
Hope Mill, Stroud,
Glos, UK, GL5 2SQ

Made in the UK